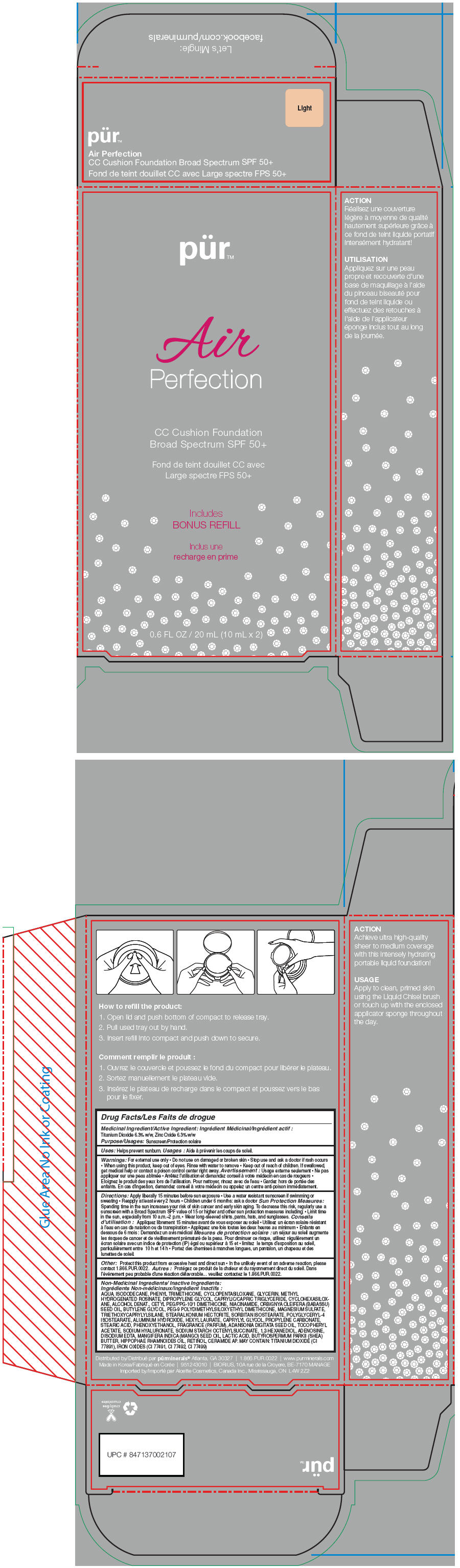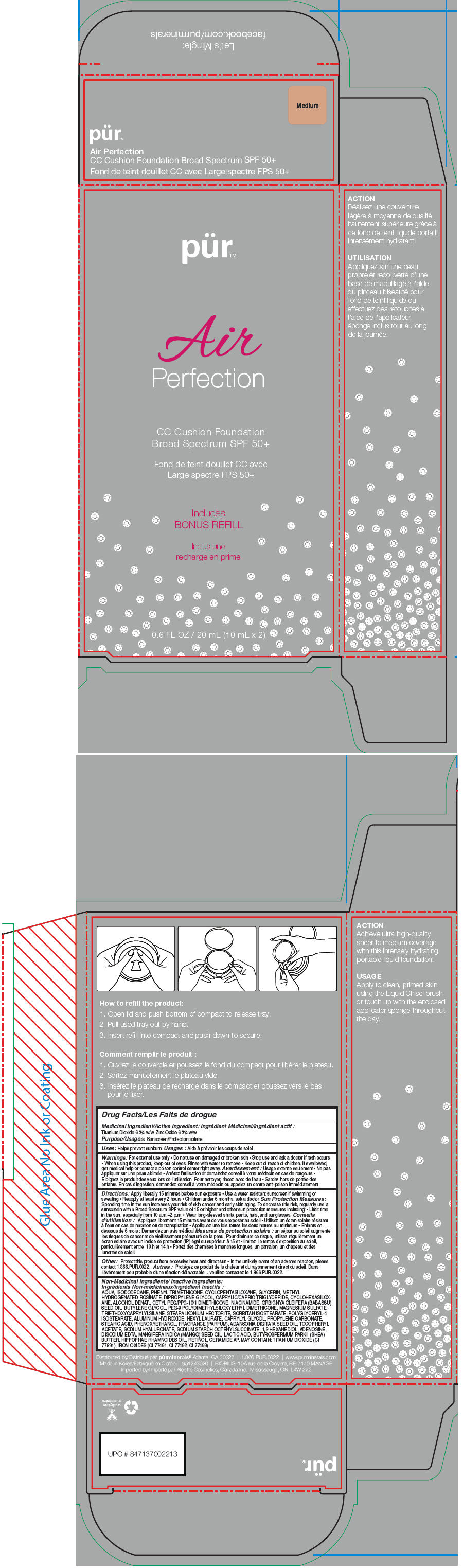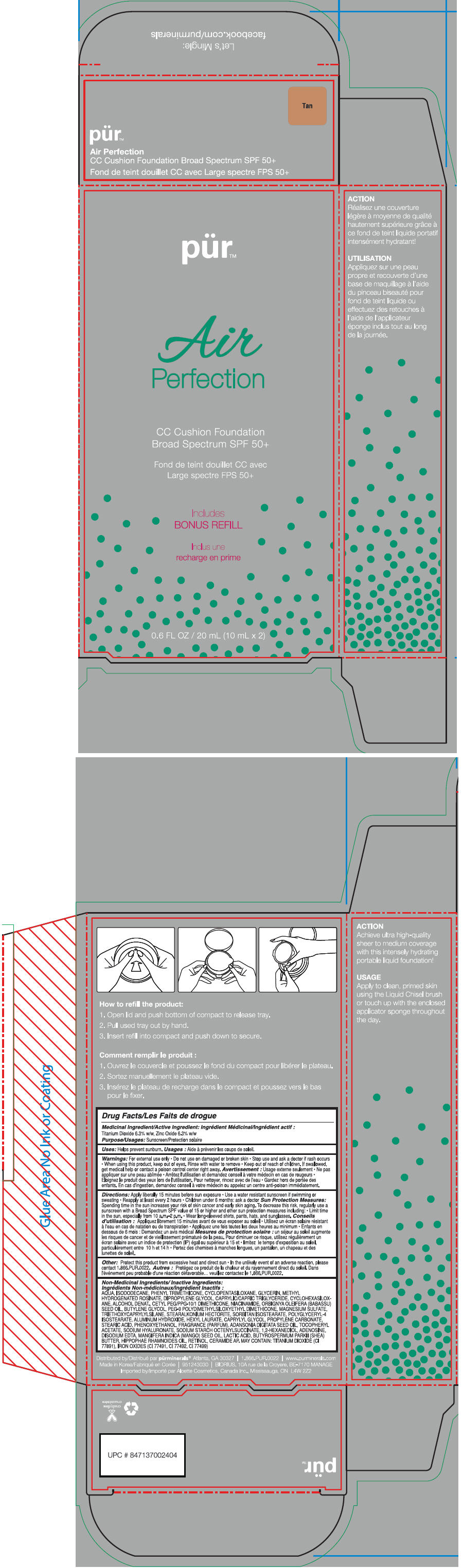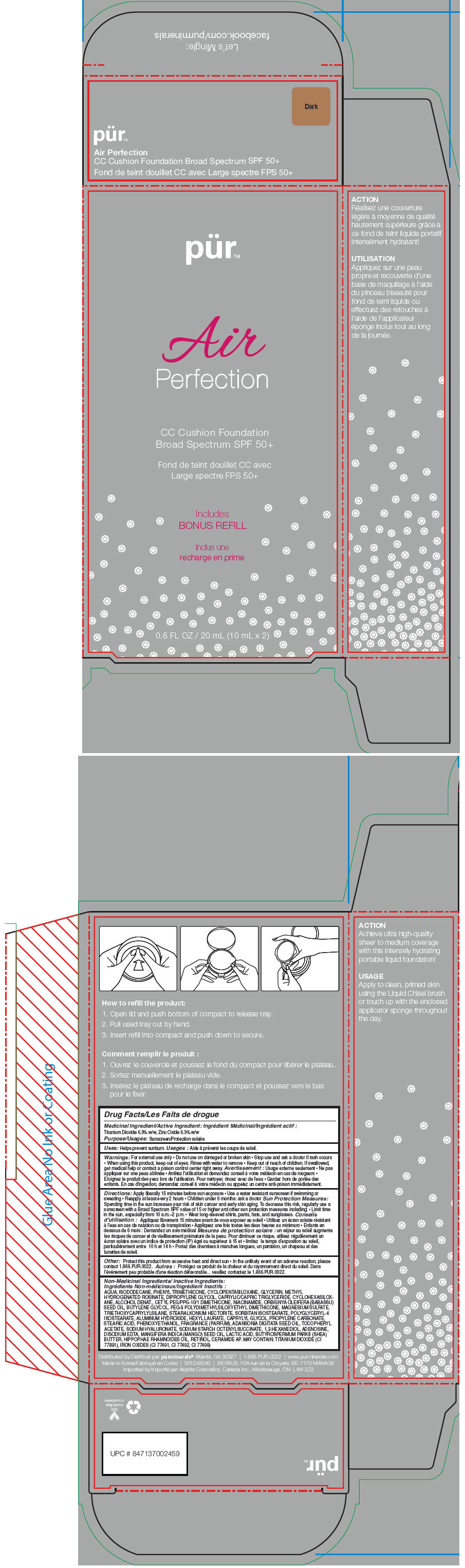 DRUG LABEL: Pur Air Perfection CC Cushion Foundation Broad Spectrum SPF 50 Plus (LIGHT)
NDC: 67345-0014 | Form: LIQUID
Manufacturer: Purminerals
Category: otc | Type: HUMAN OTC DRUG LABEL
Date: 20150109

ACTIVE INGREDIENTS: Titanium Dioxide 63 mg/1 mL; Zinc Oxide 63 mg/1 mL
INACTIVE INGREDIENTS: Water; Isododecane; Phenyl Trimethicone; Cyclomethicone 5; Glycerin; Methyl Hydrogenated Rosinate; Dipropylene Glycol; Medium-Chain Triglycerides; Cyclomethicone 6; Alcohol; Cetyl PEG/PPG-10/1 Dimethicone (HLB 4); Niacinamide; Babassu Oil; Butylene Glycol; PEG-9 Polydimethylsiloxyethyl Dimethicone; Magnesium Sulfate; Triethoxycaprylylsilane; Stearalkonium Hectorite; Sorbitan Isostearate; Polyglyceryl-4 Isostearate; Aluminum Hydroxide; Hexyl Laurate; Caprylyl Glycol; Propylene Carbonate; Stearic Acid; Phenoxyethanol; Adansonia Digitata Seed Oil; .Alpha.-Tocopherol Acetate; Hyaluronate Sodium; 1,2-Hexanediol; Adenosine; Edetate Disodium; Mango Seed Oil; Lactic Acid; Shea Butter; Hippophae Rhamnoides Seed Oil; Retinol; Ceramide 6 Ii; FERRIC OXIDE RED; FERRIC OXIDE YELLOW; FERROSOFERRIC OXIDE

Pür™ Air Perfection CC Cushion Foundation Broad Spectrum SPF 50+

Medicinal Ingredient/Active Ingredient

TITANIUM DIOXIDE 6.3% W/W, ZINC OXIDE 6.3% W/W

Purpose

Sunscreen

Uses

Helps prevent sunburn.

Warnings

For external use only

- Do not use on damaged or broken skin

- Stop use and ask a doctor if rash occurs

- When using this product, keep out of eyes. Rinse with water to remove

- Keep out of reach of children. If swallowed, get medical help or contact a poison control center right away.

Directions

Apply liberally 15 minutes before sun exposure

- Use a water resistant sunscreen if swimming or sweating
- Reapply at least every 2 hours
- Children under 6 months: ask a doctor

Sun Protection Measures

Spending time in the sun increases your risk of skin cancer and early skin aging. To decrease this risk, regularly use a sunscreen with a Broad Spectrum SPF value of 15 or higher and other sun protection measures including:

- Limit time in the sun, especially from 10 a.m.–2 p.m.
- Wear long-sleeved shirts, pants, hats, and sunglasses.

Other

Protect this product from excessive heat and direct sun

- In the unlikely event of an adverse reaction, please contact 1.866.PUR.0022.

Non-Medicinal Ingredients/ Inactive Ingredients

AQUA, ISODODECANE, PHENYL TRIMETHICONE, CYCLOPENTASILOXANE, GLYCERIN, METHYL HYDROGENATED ROSINATE, DIPROPYLENE GLYCOL, CAPRYLIC/CAPRIC TRIGLYCERIDE, CYCLOHEXASILOXANE, ALCOHOL DENAT., CETYL PEG/PPG-10/1 DIMETHICONE, NIACINAMIDE, ORBIGNYA OLEIFERA (BABASSU) SEED OIL, BUTYLENE GLYCOL, PEG-9 POLYDIMETHYLSILOXYETHYL DIMETHICONE, MAGNESIUM SULFATE, TRIETHOXYCAPRYLYLSILANE, STEARALKONIUM HECTORITE, SORBITAN ISOSTEARATE, POLYGLYCERYL-4 ISOSTEARATE, ALUMINUM HYDROXIDE, HEXYL LAURATE, CAPRYLYL GLYCOL, PROPYLENE CARBONATE, STEARIC ACID, PHENOXYETHANOL, FRAGRANCE (PARFUM), ADANSONIA DIGITATA SEED OIL, TOCOPHERYL ACETATE, SODIUM HYALURONATE, SODIUM STARCH OCTENYLSUCCINATE, 1,2-HEXANEDIOL, ADENOSINE, DISODIUM EDTA, MANGIFERA INDICA (MANGO) SEED OIL, LACTIC ACID, BUTYROSPERMUM PARKII (SHEA) BUTTER, HIPPOPHAE RHAMNOIDES OIL, RETINOL, CERAMIDE AP. MAY CONTAIN: TITANIUM DIOXIDE (CI 77891), IRON OXIDES (CI 77491, CI 77492, CI 77499)

Distributed by pürminerals®
Atlanta, GA 30327

PRINCIPAL DISPLAY PANEL - 20 mL Cartridge Carton - Light

pür™

Air
Perfection

CC Cushion Foundation
Broad Spectrum SPF 50+

Includes
BONUS REFILL

0.6 FL OZ / 20 mL (10 mL x 2)

PRINCIPAL DISPLAY PANEL - 20 mL Cartridge Carton - Medium

pür™

Air
Perfection

CC Cushion Foundation
Broad Spectrum SPF 50+

Includes
BONUS REFILL

0.6 FL OZ / 20 mL (10 mL x 2)

PRINCIPAL DISPLAY PANEL - 20 mL Cartridge Carton - Tan

pür™

Air
Perfection

CC Cushion Foundation
Broad Spectrum SPF 50+

Includes
BONUS REFILL

0.6 FL OZ / 20 mL (10 mL x 2)

PRINCIPAL DISPLAY PANEL - 20 mL Cartridge Carton - Dark

pür™

Air
Perfection

CC Cushion Foundation
Broad Spectrum SPF 50+

Includes
BONUS REFILL

0.6 FL OZ / 20 mL (10 mL x 2)